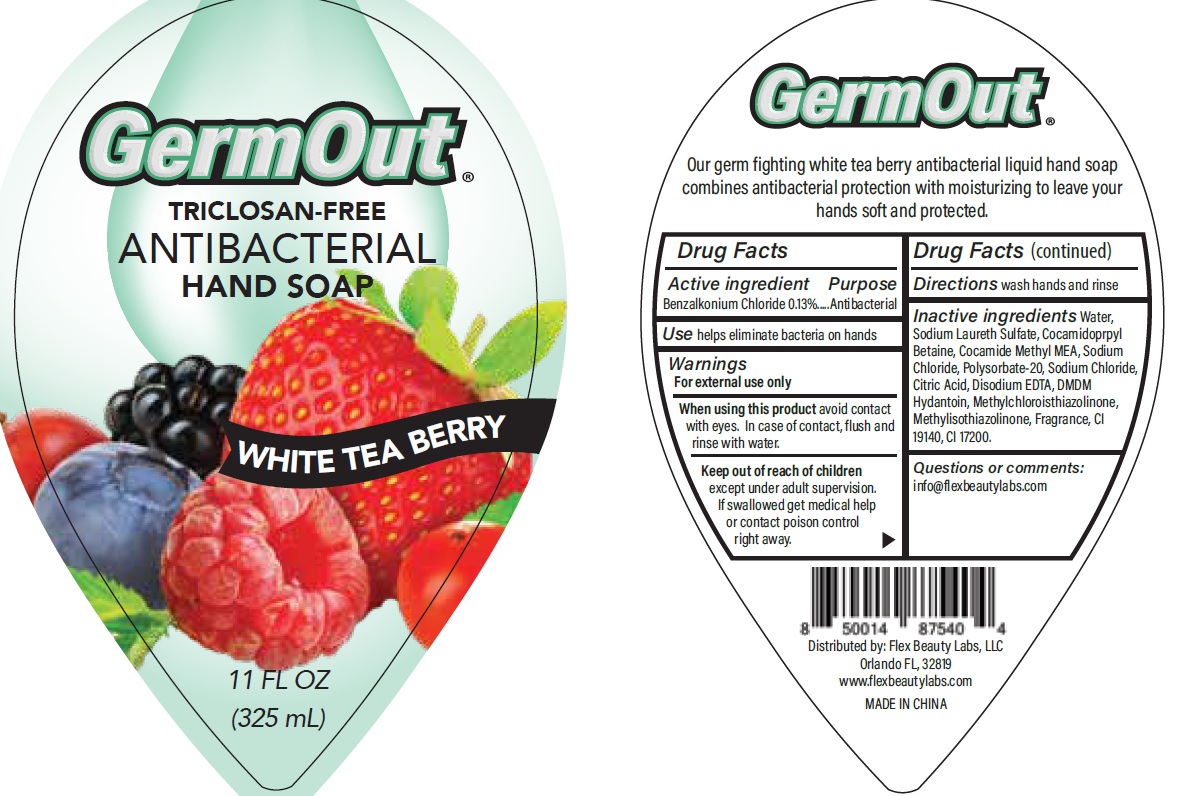 DRUG LABEL: Antibacterial
NDC: 72308-014 | Form: LIQUID
Manufacturer: Flex Beauty Labs
Category: otc | Type: HUMAN OTC DRUG LABEL
Date: 20200710

ACTIVE INGREDIENTS: BENZALKONIUM CHLORIDE 1.3 mg/1 mL
INACTIVE INGREDIENTS: WATER; SODIUM LAURETH SULFATE; COCAMIDOPROPYL BETAINE; COCOYL METHYL MONOETHANOLAMINE; SODIUM CHLORIDE; POLYSORBATE 20; EDETATE DISODIUM ANHYDROUS; METHYLCHLOROISOTHIAZOLINONE; METHYLISOTHIAZOLINONE; DMDM HYDANTOIN; BENZYL ALCOHOL; CITRIC ACID MONOHYDRATE; FD&C YELLOW NO. 5; D&C RED NO. 33

Antibacterial- Germout Hand Soap, Triclosan free, White Tea Berry

Purpose - Antibacterial

INDICATIONS AND USAGE

Use help eliminate bacteria on hands

Warnings

For external use only

Stop use and ask a doctor if irritation or redness develops

When using this product

Avoid contact with eyes.In case of contact, flush and rinse with water.

Keep out of reach of children

Except under adult supervision.

If swallowed get medical help or contact posion control right away.

Directions

Wash hands and rinse

INACTIVE INGREDIENT

Water, Sodium Laureth Sulfate, Cocamidopropyl Betaine, Sodium Chloride, Citric Acid, Coamide Methyl MEA, Fragrance, Disodium EDTA, Methylchloroisothiazolinone, Methylisothiazolinone, DMDM Hydantoin ,Cl 17200, Cl 19140.

ACTIVE INGREDIENT

Benzalkonium Chloride - 0.13%